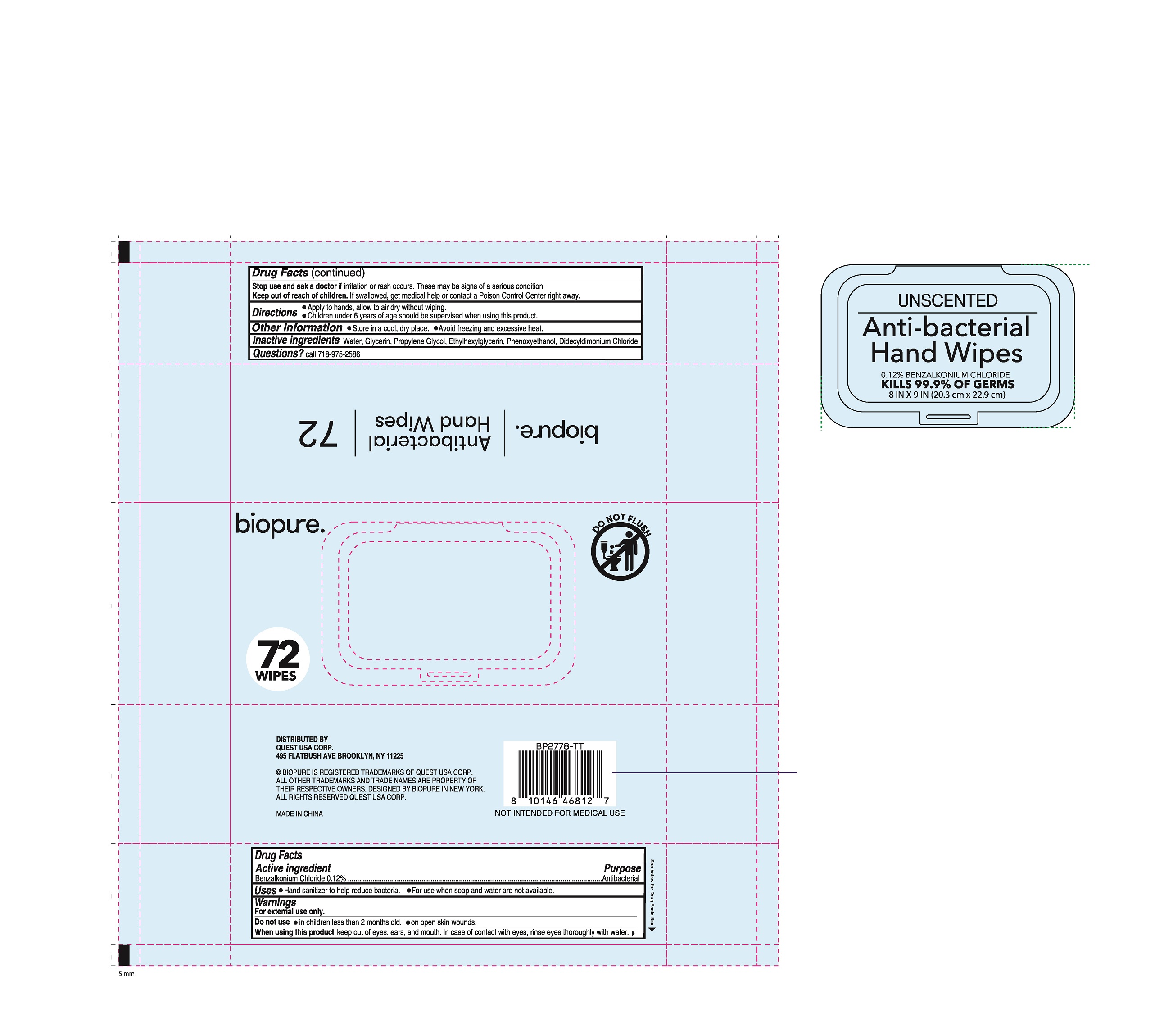 DRUG LABEL: BIOPURE 72CT ANTIBACTERIAL HAND WIPES
NDC: 83535-010 | Form: CLOTH
Manufacturer: QUANZHOU YUELIANGYUAN BIOTECHNOLOGY CO.,LTD
Category: otc | Type: HUMAN OTC DRUG LABEL
Date: 20240812

ACTIVE INGREDIENTS: BENZALKONIUM CHLORIDE 0.12 g/100 g
INACTIVE INGREDIENTS: PROPYLENE GLYCOL; GLYCERIN; PHENOXYETHANOL; WATER; ETHYLHEXYLGLYCERIN; DIDECYLDIMONIUM CHLORIDE

83535-010

Active ingredient

Benzalkonium Chloride 0.12 %

Purpose

Antibacterial

Uses

●Hand sanitizer to help reduce bacteria

●For use when soap and water are not available.

Warnings

For external use only.

Do not use

●in children less than 2 months old.

●on open skin wounds

When using this product

keep out of eyes, ears, and mouth. In case of contact with eyes, rinse eyes thoroughly with water.

Stop use and ask a doctor

if irritation or rash occurs.

These may be signs of a serious condition

Keep out of reach of children.

If swallowed. get medical help or contact a Poison Control Center right away.

Directions

●Apply to hands, allow to air dry without wiping.
●Children under 6 years of age should be supervised when using this product

Other information

●Store in a cool, dry place.

●Avoid freezing and excessive heat .

Inactive ingredients

Water , Glycerin, Propylene Glycol, Ethylhexylglycerin, Phenoxyethanol, Didecyldimonium Chloride

Question?

Call 718-975-2586